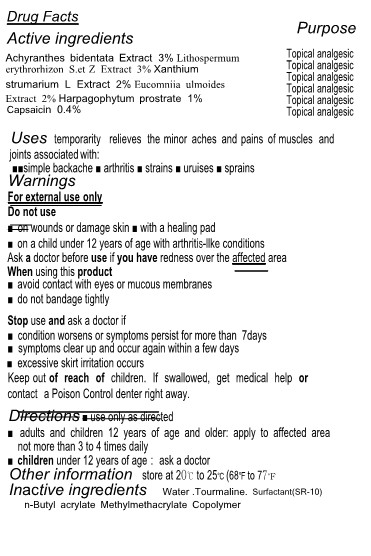 DRUG LABEL: K-Power Patch
NDC: 83404-301 | Form: PATCH
Manufacturer: BCT
Category: otc | Type: HUMAN OTC DRUG LABEL
Date: 20230413

ACTIVE INGREDIENTS: LITHOSPERMUM ERYTHRORHIZON WHOLE 3 g/100 mm; CAPSAICIN 0.4 g/100 mm; XANTHIUM STRUMARIUM LEAF 2 g/100 mm; EUCOMMIA ULMOIDES WHOLE 2 g/100 mm; HARPAGOPHYTUM PROCUMBENS WHOLE 1 g/100 mm; ACHYRANTHES BIDENTATA WHOLE 3 g/100 mm
INACTIVE INGREDIENTS: WATER; DISODIUM DECYL PHENYL ETHER DISULFONATE; BUTYL ACRYLATE/METHYL METHACRYLATE/PERFLUOROHEXYLETHYL METHACRYLATE COPOLYMER (SALUS AF); SCHORL TOURMALINE

83404-301 K-Power Patch

Active Ingredients

Achyranthes bidentata Extract 3%
Lithospermum erythrorhizon S.et Z Extract 3%
Xanthium strumarium L Extract 2%
Eucomniia ulmoides Extract 2%
Harpagophytum prostrate 1%
Capsaicin 0.4%

Purposes

Achyranthes bidentata Extract 3% --------------------------Topical analgesic
Lithospermum erythrorhizon S.et Z Extract 3% -----------Topical analgesic
Xanthium strumarium L Extract 2% -------------------------Topical analgesic
Eucomniia ulmoides Extract 2% ----------------------------Topical analgesic
Harpagophytum prostrate 1% --------------------------------Topical analgesic
Capsaicin 0.4% ----------------------------------------------- Topical analgesic

Uses

temporarity relieves the minor aches and pains of muscles and joints associated with:
■■simple backache ■ arthritis ■ strains ■ uruises ■ sprains

Warnings

For external use only

Warnings

Keep out of reach of children. If swallowed, get medical help or contact a Poison Control denter right away.

Warnings

Stop use and ask a doctor if
■ condition worsens or symptoms persist for more than 7days
■ symptoms clear up and occur again within a few days
■ excessive skirt irritation occurs

Warnings

When using this product
■ avoid contact with eyes or mucous membranes
■ do not bandage tightly

Warnings

Do not use
■ on wounds or damage skin ■ with a healing pad
■ on a child under 12 years of age with arthritiS-llke conditions
Ask a doctor before use if you have redness over the affected area

Directions

■ use only as directed
■ adults and children 12 years of age and older: apply to affected area not more than 3 to 4 times daily
■ children under 12 years of age： ask a doctor

Inactive Ingredients

Water, Tourmaline, Surfactant(SR-10), n-Butyl acrylate Methylmethacrylate Copolymer